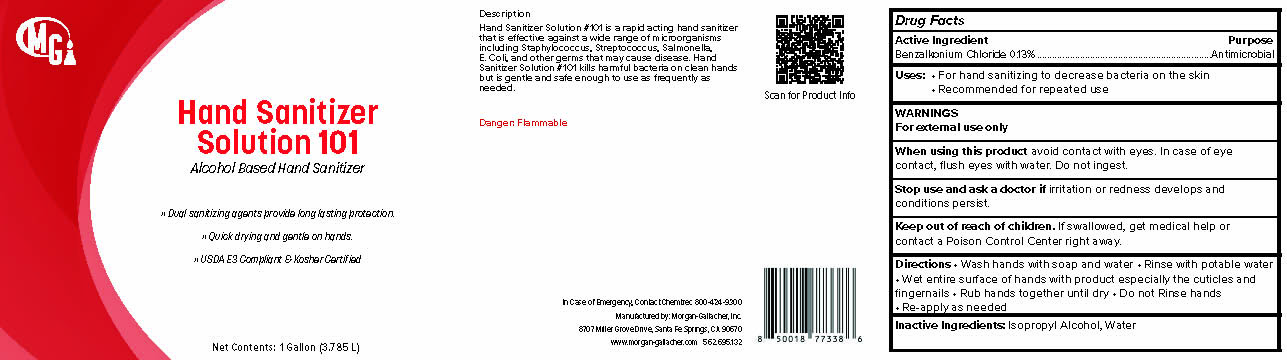 DRUG LABEL: Hand Sanitizer Solution 101
NDC: 50241-224 | Form: LIQUID
Manufacturer: Morgan Gallacher Inc. DBA Custom Chemical Formulators Inc.
Category: otc | Type: HUMAN OTC DRUG LABEL
Date: 20251223

ACTIVE INGREDIENTS: BENZALKONIUM CHLORIDE 13 kg/100 kg
INACTIVE INGREDIENTS: WATER; ISOPROPYL ALCOHOL

Hand Sanitizer Solution 101

Active Ingredient

Benzalkonium Chloride....0.13%

Purpose

Antimicrobial

Warnings

For external use only.
Flammable keep away from fire or flame

When using this product

Avoid contact with the eyes

In case of eye contact, flush eyes with water.

Stop use and ask doctor if

irritation or redness develops, if conditions persisit for more than 72 hours.

Keep out of reach of children

If swallowed, get medical help or contact a Poison Conrol Center right away

Uses

For Hand Sanitizing to decrease bacteria on the skin.

Inactive Ingredients

Water, Isopropyl Alcohol

Directions

Wash hands with soap and water. Rinse with potable water. Wet entire surface of hands with product especially the cuticles and fingernails. Rub hands together until dry. Do not rinse hands. Re-apply as needed.